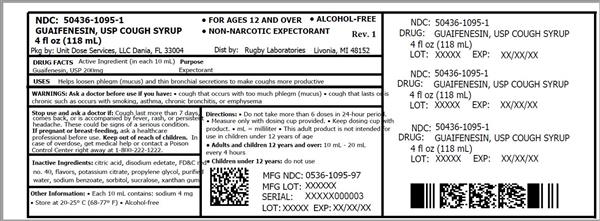 DRUG LABEL: Rugby Cough Guaifenesin
NDC: 50436-1095 | Form: LIQUID
Manufacturer: Unit Dose Services
Category: otc | Type: HUMAN OTC DRUG LABEL
Date: 20190108

ACTIVE INGREDIENTS: GUAIFENESIN 200 mg/10 mL
INACTIVE INGREDIENTS: ANHYDROUS CITRIC ACID; EDETATE DISODIUM; FD&C RED NO. 40; POTASSIUM CITRATE; PROPYLENE GLYCOL; WATER; SODIUM BENZOATE; SORBITOL; SUCRALOSE; XANTHAN GUM

Rugby Cough SYRUP Guaifenesin, 4 fl oz (118 mL)

Drug Facts

Active ingredient (in each 10 mL)

Guaifenesin, USP 200 mg

Purpose

Expectorant

Uses

helps loosen phlegm (mucus) and thin bronchial secretions to make coughs more productive

Warnings

Ask a doctor before use if you have

- cough that occurs with too much phlegm (mucus)
- cough that lasts or is chronic such as occurs with smoking, asthma, chronic bronchitis, or emphysema

Stop use and ask a doctor if cough last more than 7 days, comes back, or is accompanied by fever, rash, or persistent headache. These could be signs of a serious condition.

PREGNANCY OR BREAST FEEDING

If pregnant or breast-feeding, ask a health professional before use.

Keep out of reach of children. In case of overdose, get medical help or contact a Poison Control Center right away at 1-800-222-1222.

Directions

- do not take more than 6 doses in any 24-hour period
- measure only with dosing cup provided
- keep dosing cup with product
- mL=milliliter
- this adult product is not intended for use in children under 12 years of age

age | dose
adults and children 12 years and over | 10 mL-20 mL every 4 hours
children under 12 years | do not use

Other information

- each 10 mL contains:sodium 4 mg
- store at 20-25°C (68-77°F).
- alcohol-free

Inactive ingredients

citric acid, disodium edetate , FD&C red no. 40, flavors, potassium citrate, propylene glycol, purified water, sodium benzoate, sorbitol, sucralose, xanthan gum.

Questions?

1-866-467-2748

Distributed by:
Rugby Laboratories

31778 Enterprise Drive

Livonia, MI 48150

www.rugbylaboratories.com

Re-order No.370448

Rev.10/15

R-107

HOW SUPPLIED

Product: 50436-1095

NDC: 50436-1095-1 1 mL in a CARTON / 118 in a BOTTLE